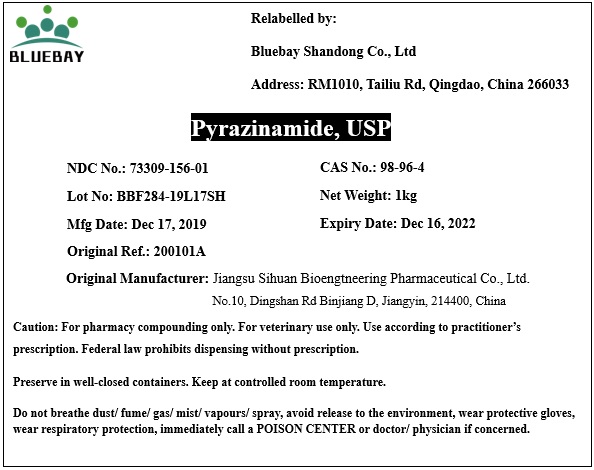 DRUG LABEL: Pyrazinamide
NDC: 73309-156 | Form: POWDER
Manufacturer: BLUEBAY SHANDONG CO.,LTD
Category: other | Type: BULK INGREDIENT
Date: 20200702

ACTIVE INGREDIENTS: PYRAZINAMIDE 1 kg/1 kg

Pyrazinamide